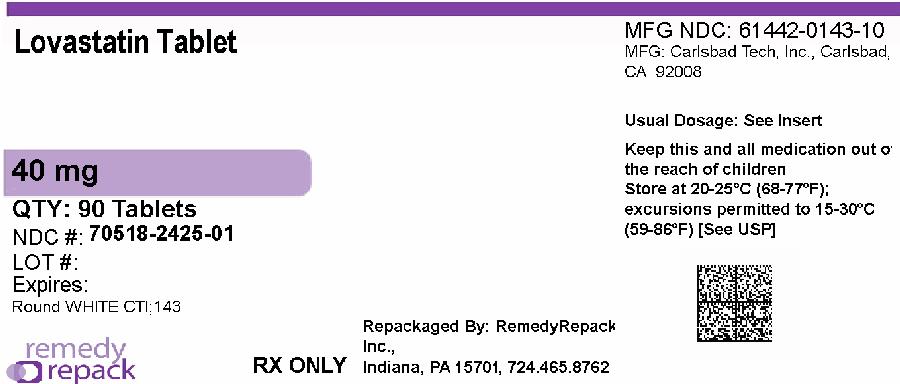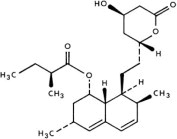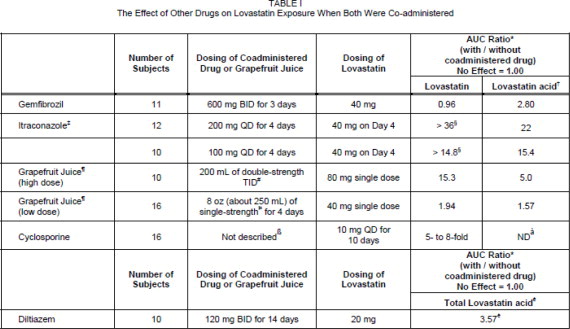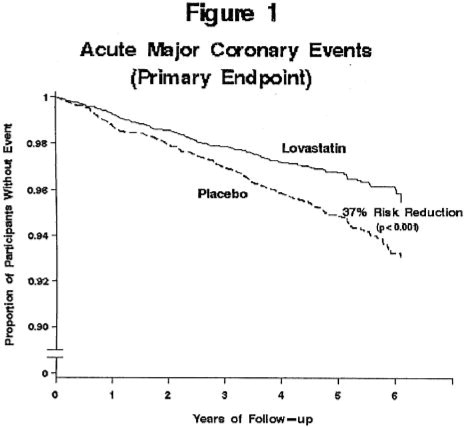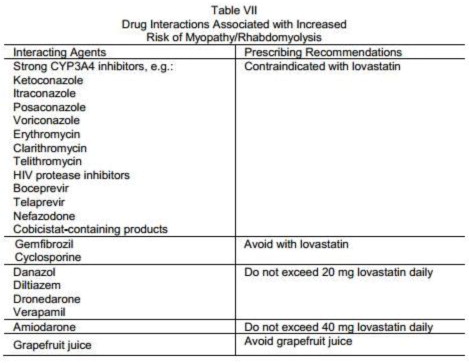 DRUG LABEL: Lovastatin
NDC: 70518-2425 | Form: TABLET
Manufacturer: REMEDYREPACK INC.
Category: prescription | Type: HUMAN PRESCRIPTION DRUG LABEL
Date: 20260205

ACTIVE INGREDIENTS: LOVASTATIN 40 mg/1 1
INACTIVE INGREDIENTS: MAGNESIUM STEARATE; CELLULOSE, MICROCRYSTALLINE; POLOXAMER 188; SODIUM STARCH GLYCOLATE TYPE A POTATO; STARCH, CORN; TALC; BUTYLATED HYDROXYANISOLE; LACTOSE MONOHYDRATE

Lovastatin Tablet USP

Rx only

DESCRIPTION

Lovastatin is a cholesterol lowering agent isolated from a strain of Aspergillus terreus.After oral ingestion, lovastatin, which is an inactive lactone, is hydrolyzed to the corresponding β-hydroxyacid form. This is a principal metabolite and an inhibitor of 3-hydroxy-3-methylglutaryl-coenzyme A (HMG-CoA) reductase. This enzyme catalyzes the conversion of HMG-CoA to mevalonate, which is an early and rate limiting step in the biosynthesis of cholesterol.

Lovastatin is [1 S -[1α(R*), 3α, 7β, 8β(2 S *,4 S *),8aβ]]-1,2,3, 7,8,8a-hexahydro-3,7-dimethyl-8-[2-(tetrahydro-4-hydroxy-6-oxo-2 H-pyran-2-yl)ethyl]-1-naphthalenyl 2-methylbutanoate. The empirical formula of lovastatin is C24H36O5and its molecular weight is 404.55. Its structural formula is:

Lovastatin is a white, nonhygroscopic crystalline powder that is insoluble in water and sparingly soluble in ethanol, methanol, and acetonitrile.

Lovastatin tablets are supplied as 10 mg, 20 mg and 40 mg tablets for oral administration. In addition to the active ingredient lovastatin, each tablet contains the following inactive ingredients: lactose monohydrate, magnesium stearate, microcrystalline cellulose, poloxamer, pregelatinized starch, sodium starch glycolate, butylated hydroxyanisole and talc. Butylated hydroxyanisole (BHA) is added as a preservative.

Clinical Pharmacology

The involvement of low-density lipoprotein cholesterol (LDL-C) in atherogenesis has been well-documented in clinical and pathological studies, as well as in many animal experiments. Epidemiological and clinical studies have established that high LDL-C and low high-density lipoprotein cholesterol (HDL-C) are both associated with coronary heart disease. However, the risk of developing coronary heart disease is continuous and graded over the range of cholesterol levels and many coronary events do occur in patients with total cholesterol (total-C) and LDL-C in the lower end of this range.

Lovastatin has been shown to reduce both normal and elevated LDL-C concentrations. LDL is formed from very low-density lipoprotein (VLDL) and is catabolized predominantly by the high affinity LDL receptor. The mechanism of the LDL-lowering effect of lovastatin may involve both reduction of VLDL-C concentration, and induction of the LDL receptor, leading to reduced production and/or increased catabolism of LDL-C. Apolipoprotein B also falls during treatment with lovastatin.

Lovastatin is a specific inhibitor of HMG-CoA reductase, the enzyme which catalyzes the conversion of HMG-CoA to mevalonate. The conversion of HMG-CoA to mevalonate is an early step in the biosynthetic pathway for cholesterol.

Pharmacokinetics

Lovastatin is a lactone, which is readily hydrolyzed in vivoto the corresponding β-hydroxyacid, a strong. inhibitor of HMG-CoA reductase. Inhibition of HMG-CoA reductase is the basis for an assay in pharmacokinetic studies of the β-hydroxyacid metabolites (active inhibitors) and, following base hydrolysis, active plus latent inhibitors (total inhibitors) in plasma following administration of lovastatin.

Following an oral dose of^14C-labeled lovastatin in man, 10% of the dose was excreted in urine and 83% in feces. The latter represents absorbed drug equivalents excreted in bile, as well as any unabsorbed drug. Plasma concentrations of total radioactivity (lovastatin plus^14C-metabolites) peaked at 2 hours and declined rapidly to about 10% of peak by 24 hours postdose. Absorption of lovastatin, estimated relative to an intravenous reference dose, in each of four animal species tested, averaged about 30% of an oral dose. In animal studies, after oral dosing, lovastatin had high selectivity for the liver, where it achieved substantially higher concentrations than in non-target tissues. Lovastatin undergoes extensive first-pass extraction in the liver, its primary site of action, with subsequent excretion of drug equivalents in the bile. As a consequence of extensive hepatic extraction of lovastatin, the availability of drug to the general circulation is low and variable. In a single dose study in four hypercholesterolemic patients, it was estimated that less than 5% of an oral dose of lovastatin reaches the general circulation as active inhibitors. Following administration of lovastatin tablets the coefficient of variation, based on between-subject variability, was approximately 40% for the area under the curve (AUC) of total inhibitory activity in the general circulation.

Both lovastatin and its β-hydroxyacid metabolite are highly bound (>95%) to human plasma proteins. Animal studies demonstrated that lovastatin crosses the blood-brain and placental barriers.

The major active metabolites present in human plasma are the β-hydroxyacid of lovastatin, its 6'-hydroxy derivative, and two additional metabolites. Peak plasma concentrations of both active and total inhibitors were attained within 2 to 4 hours of dose administration. While the recommended therapeutic dose range is 10 to 80 mg/day, linearity of inhibitory activity in the general circulation was established by a single dose study employing lovastatin tablet dosages from 60 to as high as 120 mg. With a once-a-day dosing regimen, plasma concentrations of total inhibitors over a dosing interval achieved a steady state between the second and third days of therapy and were about 1.5 times those following a single dose. When lovastatin was given under fasting conditions, plasma concentrations of total inhibitors were on average about two-thirds those found when lovastatin was administered immediately after a standard test meal.

In a study of patients with severe renal insufficiency (creatinine clearance 10 to 30 mL/min), the plasma concentrations of total inhibitors after a single dose of lovastatin were approximately two-fold higher than those in healthy volunteers.

In a study including 16 elderly patients between 70 to 78 years of age who received lovastatin 80 mg/day, the mean plasma level of HMG-CoA reductase inhibitory activity was increased approximately 45% compared with 18 patients between 18 to 30 years of age (see PRECAUTIONS, Geriatric Use).

Although the mechanism is not fully understood, cyclosporine has been shown to increase the AUC of HMG-CoA reductase inhibitors. The increase in AUC for lovastatin and lovastatin acid is presumably due, in part, to inhibition of CYP3A4.

The risk of myopathy is increased by high levels of HMG-CoA reductase inhibitory activity in plasma. Strong inhibitors of CYP3A4 can raise the plasma levels of HMG-CoA reductase inhibitory activity and increase the risk of myopathy (see WARNINGS, Myopathy/Rhabdomyolysisand PRECAUTIONS, Drug Interactions).

Lovastatin is a substrate for cytochrome P450 isoform 3A4 (CYP3A4) (see PRECAUTIONS, Drug Interactions.) Grapefruit juice contains one or more components that inhibit CYP3A4 and can increase the plasma concentrations of drugs metabolized by CYP3A4. In one study^1, 10 subjects consumed 200 mL of double-strength grapefruit juice (one can of frozen concentrate diluted with one rather than 3 cans of water) three times daily for 2 days and an additional 200 mL double-strength grapefruit juice together with and 30 and 90 minutes following a single dose of 80 mg lovastatin on the third day. This regimen of grapefruit juice resulted in a mean increase in the serum concentration of lovastatin and its β-hydroxyacid metabolite (as measured by the area under the concentration-time curve) of 15-fold and 5-fold, respectively [as measured using a chemical assay-high performance liquid chromatography.] In a second study, 15 subjects consumed one 8 oz glass of single-strength grapefruit juice (one can of frozen concentrate diluted with 3 cans of water) with breakfast for 3 consecutive days and a single dose of 40 mg lovastatin in the evening of the third day. This regimen of grapefruit juice resulted in a mean increase in the plasma concentration (as measured by the area under the concentration-time curve) of active and total HMG-CoA reductase inhibitory activity [using an enzyme inhibition assay both before (for active inhibitors) and after (for total inhibitors) base hydrolysis] of 1.34-fold and 1.36-fold, respectively, and of lovastatin and its β-hydroxyacid metabolite [measured using a chemical assay-liquid chromatography/tandem mass spectrometry-different from that used in the first^1study] of 1.94-fold and 1.57-fold, respectively. The effect of amounts of grapefruit juice between those used in these two studies on lovastatin pharmacokinetics has not been studied.

____________________________________

^1Kantola, T, et al., Clin Pharmacol Ther 1998; 63(4):397-402.

* Results based on a chemical assay.

† Lovastatin acid refers to the β-hydroxyacid of lovastatin.

‡ The mean total AUC of lovastatin without itraconazole phase could not be determined accurately. Results could be representative of strong CYP3A4 inhibitors such as ketoconazole, posaconazole, clarithromycin, telithromycin, HIV protease inhibitors, and nefazodone.

§ Estimated minimum change.

¶ The effect of amounts of grapefruit juice between those used in these two studies on lovastatin pharmacokinetics has not been studied.

# Double-strength: one can of frozen concentrate diluted with one can of water.

Grapefruit juice was administered TID for 2 days, and 200 mL together with single dose lovastatin and 30 and 90 minutes following single dose lovastatin on Day 3.

Þ Single-strength: one can of frozen concentrate diluted with 3 cans of water. Grapefruit juice was administered with breakfast for 3 days, and lovastatin was administered in the evening on Day 3.

ß Cyclosporine-treated patients with psoriasis or post kidney or heart transplant patients with stable graft function, transplanted at least 9 months prior to study.

à ND = Analyte not determined.

è Lactone converted to acid by hydrolysis prior to analysis. Figure represents total unmetabolized acid and lactone.

Clinical Studies in Adults

Lovastatin has been shown to reduce total-C and LDL-C in heterozygous familial and non-familial forms of primary hypercholesterolemia and in mixed hyperlipidemia. A marked response was seen within 2 weeks, and the maximum therapeutic response occurred within 4 to 6 weeks. The response was maintained during continuation of therapy. Single daily doses given in the evening were more effective than the same dose given in the morning, perhaps because cholesterol is synthesized mainly at night.

In multicenter, double-blind studies in patients with familial or non-familial hypercholesterolemia, lovastatin, administered in doses ranging from 10 mg q.p.m. to 40 mg b.i.d., was compared to placebo. Lovastatin significantly decreased plasma total-C, LDL-C, total-C/HDL-C ratio and LDL-C/HDL-C ratio. In addition, lovastatin produced increases of variable magnitude in HDL-C, and modestly decreased VLDL-C and plasma TG (see Tables IIthrough IVfor dose response results).

The results of a study in patients with primary hypercholesterolemia are presented in Table II.

TABLE II Lovastatin vs Placebo (Mean Percent Change from Baseline After 6 Weeks)
DOSAGE | N | TOTAL-C | LDL-C | HDL-C | LDL-C/ HDL-C | TOTAL-C/ HDL/C | TRIG.
Placebo | 33 | -2 | -1 | -1 | 0 | +1 | +9
Lovastatin
10 mg q.p.m. | 33 | -16 | -21 | +5 | -24 | -19 | -10
20 mg q.p.m. | 33 | -19 | -27 | +6 | -30 | -23 | +9
10 mg b.i.d. | 32 | -19 | -28 | +8 | -33 | -25 | -7
40 mg q.p.m. | 33 | -22 | -31 | +5 | -33 | -25 | -8
20 mg b.i.d. | 36 | -24 | -32 | +2 | -32 | -24 | -6

Lovastatin was compared to cholestyramine in a randomized open parallel study. The study was performed with patients with hypercholesterolemia who were at high risk of myocardial infarction. Summary results are presented in Table III.

TABLE III Lovastatin vs. Cholestyramine (Percent Change from Baseline After 12 Weeks)
TREATMENT | N | TOTAL-C (mean) | LDL-C (mean) | HDL-C (mean) | LDL-C/ HDL-C (mean) | TOTAL-C/ HDL-C (mean) | VLDL-C (median) | TRIG. (median)
Lovastatin
20 mg b.i.d. | 85 | -27 | -32 | +9 | -36 | -31 | -34 | -21
40 mg b.i.d. | 88 | -34 | -42 | +8 | -44 | -37 | -31 | -27
Cholestyramine
12 g b.i.d. | 88 | -17 | -23 | +8 | -27 | -21 | +2 | +11

Lovastatin was studied in controlled trials in hypercholesterolemic patients with well-controlled non-insulin dependent diabetes mellitus with normal renal function. The effect of lovastatin on lipids and lipoproteins and the safety profile of lovastatin were similar to that demonstrated in studies in nondiabetics. Lovastatin had no clinically important effect on glycemic control or on the dose requirement of oral hypoglycemic agents.

Expanded Clinical Evaluation of Lovastatin (EXCEL) Study

Lovastatin was compared to placebo in 8,245 patients with hypercholesterolemia (total-C 240-300 mg/dL [6.2 mmol/L-7.6 mmol/L], LDL-C >160 mg/dL [4.1 mmol/L]) in the randomized, double-blind, parallel, 48-week EXCEL study. All changes in the lipid measurements (Table IV) in lovastatin treated patients were dose-related and significantly different from placebo (p≤0.001). These results were sustained throughout the study.

TABLE IV Lovastatin vs. Placebo (Percent Change from Baseline-- Average Values Between Weeks 12 and 48)
DOSAGE | N** | TOTAL-C (mean) | LDL-C (mean) | HDL-C (mean) | LDL-C/ HDL-C (mean) | TOTAL-C/ HDL-C (mean) | TRIG. (median)
Placebo | 1663 | +0.7 | +0.4 | +2.0 | +0.2 | +0.6 | +4
Lovastatin
20 mg q.p.m. | 1642 | -17 | -24 | +6.6 | -27 | -21 | -10
40 mg q.p.m. | 1645 | -22 | -30 | +7.2 | -34 | -26 | -14
20 mg b.i.d. | 1646 | -24 | -34 | +8.6 | -38 | -29 | -16
40 mg b.i.d. | 1649 | -29 | -40 | +9.5 | -44 | -34 | -19
**Patients enrolled

Air Force/Texas Coronary Atherosclerosis Prevention Study (AFCAPS/TexCAPS)

The Air Force/Texas Coronary Atherosclerosis Prevention Study (AFCAPS/TexCAPS), a double-blind, randomized, placebo-controlled, primary prevention study, demonstrated that treatment with lovastatin decreased the rate of acute major coronary events (composite endpoint of myocardial infarction, unstable angina, and sudden cardiac death) compared with placebo during a median of 5.1 years of follow-up. Participants were middle-aged and elderly men (ages 45 to 73) and women (ages 55 to 73) without symptomatic cardiovascular disease with average to moderately elevated total-C and LDL-C, below average HDL-C, and who were at high risk based on elevated total-C/HDL-C. In addition to age, 63% of the participants had at least one other risk factor (baseline HDL-C <35 mg/dL, hypertension, family history, smoking and diabetes).

AFCAPS/TexCaps enrolled 6,605 participants (5,608 men, 997 women) based on the following lipid entry criteria: total-C range of 180 to 264 mg/dL, LDL-C range of 130 to 190 mg/dL, HDL-C of ≤45 mg/dL for men and ≤47 mg/dL for women, and TG of ≤400 mg/dL. Participants were treated with standard care, including diet, and either lovastatin 20 to 40 mg daily (n= 3,304) or placebo (n= 3,301). Approximately 50% of the participants treated with lovastatin were titrated to 40 mg daily when their LDL-C remained >110 mg/dL at the 20-mg starting dose.

Lovastatin reduced the risk of a first acute major coronary event, the primary efficacy endpoint, by 37% (lovastatin 3.5%, placebo 5.5%; p<0.001; Figure 1). A first acute major coronary event was defined as myocardial infarction (54 participants on lovastatin, 94 on placebo) or unstable angina (54 vs. 80) or sudden cardiac death (8 vs. 9). Furthermore, among the secondary endpoints, lovastatin reduced the risk of unstable angina by 32% (1.8 vs. 2.6%; p=0.023), of myocardial infarction by 40% (1.7 vs. 2.9%; p=0.002), and of undergoing coronary revascularization procedures (e.g., coronary artery bypass grafting or percutaneous transluminal coronary angioplasty) by 33% (3.2 vs. 4.8%; p=0.001). Trends in risk reduction associated with treatment with lovastatin were consistent across men and women, smokers and non-smokers, hypertensives and non-hypertensives, and older and younger participants. Participants with ≥2 risk factors had risk reductions (RR) in both acute major coronary events (RR 43%) and coronary revascularization procedures (RR 37%). Because there were too few events among those participants with age as their only risk factor in this study, the effect of lovastatin on outcomes could not be adequately assessed in this subgroup.

Atherosclerosis

In the Canadian Coronary Atherosclerosis Intervention Trial (CCAIT), the effect of therapy with lovastatin on coronary atherosclerosis was assessed by coronary angiography in hyperlipidemic patients. In the randomized, double-blind, controlled clinical trial, patients were treated with conventional measures (usually diet and 325 mg of aspirin every other day) and either lovastatin 20 to 80 mg daily or placebo. Angiograms were evaluated at baseline and at two years by computerized quantitative coronary angiography (QCA). Lovastatin significantly slowed the progression of lesions as measured by the mean change per-patient in minimum lumen diameter (the primary endpoint) and percent diameter stenosis, and decreased the proportions of patients categorized with disease progression (33% vs. 50%) and with new lesions (16% vs. 32%).

In a similarly designed trial, the Monitored Atherosclerosis Regression Study (MARS), patients were treated with diet and either lovastatin 80 mg daily or placebo. No statistically significant difference between lovastatin and placebo was seen for the primary endpoint (mean change per patient in percent diameter stenosis of all lesions), or for most secondary QCA endpoints. Visual assessment by angiographers who formed a consensus opinion of overall angiographic change (Global Change Score) was also a secondary endpoint. By this endpoint, significant slowing of disease was seen, with regression in 23% of patients treated with lovastatin compared to 11% of placebo patients.

In the Familial Atherosclerosis Treatment Study (FATS), either lovastatin or niacin in combination with a bile acid sequestrant for 2.5 years in hyperlipidemic subjects significantly reduced the frequency of progression and increased the frequency of regression of coronary atherosclerotic lesions by QCA compared to diet and, in some cases, low-dose resin.

The effect of lovastatin on the progression of atherosclerosis in the coronary arteries has been corroborated by similar findings in another vasculature. In the Asymptomatic Carotid Artery Progression Study (ACAPS), the effect of therapy with lovastatin on carotid atherosclerosis was assessed by B-mode ultrasonography in hyperlipidemic patients with early carotid lesions and without known coronary heart disease at baseline. In this double-blind, controlled clinical trial, 919 patients were randomized in a 2 x 2 factorial design to placebo, lovastatin 10 to 40 mg daily and/or warfarin. Ultrasonograms of the carotid walls were used to determine the change per patient from baseline to three years in mean maximum intimal-

medial thickness (IMT) of 12 measured segments. There was a significant regression of carotid lesions in patients receiving lovastatin alone compared to those receiving placebo alone (p=0.001). The predictive value of changes in IMT for stroke has not yet been established. In the lovastatin group there was a significant reduction in the number of patients with major cardiovascular events relative to the placebo group (5 vs. 14) and a significant reduction in all-cause mortality (1 vs. 8).

Efficacy of Lovastatin in Adolescent Boys with Heterozygous Familial Hypercholesterolemia

In a double-blind, placebo-controlled study, 132 boys 10 to 17 years of age (mean age 12.7 yrs) with heterozygous familial hypercholesterolemia (heFH) were randomized to lovastatin (n=67) or placebo (n=65) for 48 weeks. Inclusion in the study required a baseline LDL-C level between 189 and 500 mg/dL and at least one parent with an LDL-C level >189 mg/dL. The mean baseline LDL-C value was 253.1 mg/dL (range: 171 to 379 mg/dL) in the lovastatin group compared to 248.2 mg/dL (range 158.5 to 413.5 mg/dL) in the placebo group. The dosage of lovastatin (once daily in the evening) was 10 mg for the first 8 weeks, 20 mg for the second 8 weeks, and 40 mg thereafter.

Lovastatin significantly decreased plasma levels of total-C, LDL-C and apolipoprotein B (see Table V).

TABLE V Lipid-lowering Effects of Lovastatin in Adolescent Boys with Heterozygous Familial Hypercholesterolemia (Mean Percent Change from Baseline at week 48 in Intention-to-Treat Population)
DOSAGE | N | TOTAL-C | LDL-C | HDL-C | TG. * | Apolipoprotein B
Placebo | 61 | -1.1 | -1.4 | -2.2 | -1.4 | -4.4
Lovastatin | 64 | -19.3 | -24.2 | +1.1 | -1.9 | -21
*data presented as median percent changes

The mean achieved LDL-C value was 190.9 mg/dL (range: 108 to 336 mg/dL) in the lovastatin group compared to 244.8 mg/dL (range: 135 to 404 mg/dL) in the placebo group.

Efficacy of Lovastatin in Post-menarchal Girls with Heterozygous Familial Hypercholesterolemia

In a double-blind, placebo-controlled study, 54 girls 10 to 17 years of age who were at least 1 year post-menarche with heFH were randomized to lovastatin (n=35) or placebo (n=19) for 24 weeks. Inclusion in the study required a baseline LDL-C level of 160 to 400 mg/dL and a parental history of familial hypercholesterolemia. The mean baseline LDL-C value was 218.3 mg/dL (range: 136.3 to 363.7 mg/dL) in the lovastatin group compared to 198.8 mg/dL (range: 151.5 to 283.1 mg/dL) in the placebo group. The dosage of lovastatin (once daily in the evening) was 20 mg for the first 4 weeks, and 40 mg thereafter.

Lovastatin significantly decreased plasma levels of total-C, LDL-C, and apolipoprotein B (see Table VI).

TABLE VI Lipid-lowering Effects of Lovastatin in Post-menarchal Girls with Heterozygous Familial Hypercholesterolemia (Mean Percent Change from Baseline at Week 24 in Intention-to-Treat Population)
DOSAGE | N | TOTAL-C | LDL-C | HDL-C | TG. * | Apolipoprotein B
Placebo | 18 | +3.6 | +2.5 | +4.8 | -3.0 | +6.4
Lovastatin | 35 | -22.4 | -29.2 | +2.4 | -22.7 | -24.4
*data presented as median percent changes

The mean achieved LDL-C value was 154.5 mg/dL (range: 82 to 286 mg/dL) in the lovastatin group compared to 203.5 mg/dL (range: 135 to 304 mg/dL) in the placebo group.

The safety and efficacy of doses above 40 mg daily have not been studied in children. The long-term efficacy of lovastatin therapy in childhood to reduce morbidity and mortality in adulthood has not been established.

Eye

There was a high prevalence of baseline lenticular opacities in the patient population included in the early clinical trials with lovastatin. During these trials the appearance of new opacities was noted in both the lovastatin and placebo groups. There was no clinically significant change in visual acuity in the patients who had new opacities reported nor was any patient, including those with opacities noted at baseline, discontinued from therapy because of a decrease in visual acuity.

A three-year, double-blind, placebo-controlled study in hypercholesterolemic patients to assess the effect of lovastatin on the human lens demonstrated that there were no clinically or statistically significant differences between the lovastatin and placebo groups in the incidence, type or progression of lenticular opacities. There are no controlled clinical data assessing the lens available for treatment beyond three years.

Indications and Usage

Therapy with lovastatin should be a component of multiple risk factor intervention in those individuals with dyslipidemia at risk for atherosclerotic vascular disease. Lovastatin should be used in addition to a diet restricted in saturated fat and cholesterol as part of a treatment strategy to lower total-C and LDL-C to target levels when the response to diet and other nonpharmacological measures alone has been inadequate to reduce risk.

Primary Prevention of Coronary Heart Disease

In individuals without symptomatic cardiovascular disease, average to moderately elevated total-C and LDL-C, and below average HDL-C, lovastatin is indicated to reduce the risk of:

- Myocardial infarction
- Unstable angina
- Coronary revascularization procedures

(See CLINICAL PHARMACOLOGY, Clinical Studies.)

Coronary Heart Disease

Lovastatin is indicated to slow the progression of coronary atherosclerosis in patients with coronary heart disease as part of a treatment strategy to lower total-C and LDL-C to target levels.

Hypercholesterolemia

Therapy with lipid-altering agents should be a component of multiple risk factor intervention in those individuals at significantly increased risk for artherosclerotic vascular disease due to hypercholesterolemia. Lovastatin is indicated as an adjunct to diet for the reduction of elevated total-C and LDL-C levels in patients with primary hypercholesterolemia (Types IIa and IIb^2), when the response to diet restricted in saturated fat and cholesterol and to other nonpharmacological measures alone has been inadequate.

^2Classification of Hyperlipoproteinemias
 |  |  | Lipid Elevaions
Type |  | Lipoproteins; elevated | major | minor
I |  | chylonicrons | TG | ↑→C
IIa |  | LDL | C | --
IIb |  | LDL, VLDL | C | TG
III | (rare) | IDL | C/TG | --
IV |  | VLDL | TG | ↑→C
V | (rare) | chylomicrons, VLDL | TG | ↑→C
IDL = intermediate-densit lipoprotein

Adolescent Patients with Heterozygous Familial Hypercholesterolemia

Lovastatin is indicated as an adjunct to diet to reduce total-C, LDL-C and apolipoprotein B levels in adolescent boys and girls who are at least one year post-menarche, 10 to 17 years of age, with heFH if after an adequate trial of diet therapy the following findings are present:

1. LDL-C remains >189 mg/dL or
2. LDL-C remains >160 mg/dL and:
  - there is a positive family history of premature cardiovascular disease or
  - two or more other CVD risk factors are present in the adolescent patient

General Recommendations

Prior to initiating therapy with lovastatin, secondary causes for hypercholesterolemia (e.g., poorly controlled diabetes mellitus, hypothyroidism, nephrotic syndrome, dysproteinemias, obstructive liver disease, other drug therapy, alcoholism) should be excluded, and a lipid profile performed to measure total-C, HDL-C, and TG. For patients with TG less than 400 mg/dL (<4.5 mmol/L), LDL-C can be estimated using the following equation:

LDL-C = total-C - [0.2 × (TG) + HDL-C]

For TG levels >400 mg/dL (>4.5 mmol/L), this equation is less accurate and LDL-C concentrations should be determined by ultracentrifugation. In hypertriglyceridemic patients, LDL-C may be low or normal despite elevated total-C. In such cases, lovastatin is not indicated.

The National Cholesterol Education Program (NCEP) Treatment Guidelines are summarized below:

NCEP Treatment Guidelines: LDL-C Goals and Cutpoints for Therapeutic Lifestyle Changes and Drug Therapy in Different Risk Categories
Risk Category | LDL Goal; (mg/dL) | LDL Level at Which to; Initiate Therapeutic; Lifestyle Changes; (mg/dL) | LDL Level at Which to; Consider Drug Therapy; (mg/dL)
CHD† or CHD risk equivalents; (10-year risk >20%) | <100 | ≥100 | ≥130 (100 to 129:; drug optional) ††
2+ Risk factors; (10 year risk ≤20%) | <130 | ≥130 | 10-year risk; 10 to 20%: ≥130; 10-year risk; <10%: ≥160
0 to 1 Risk factor ††† | <160 | ≥160 | ≥190; (160 to 189: LDL-lowering; drug optional)
† CHD, coronary heart disease
†† Some authorities recommend use of LDL-lowering drugs in this category if an LDL-C level of <100 mg/dL cannot be achieved by therapeutic lifestyle changes. Others prefer use of drugs that primarily modify triglycerides and HDL-C, e.g., nicotinic acid or fibrate. Clinical judgment also may call for deferring drug therapy in this subcategory.
††† Almost all people with 0 to 1 risk factor have a 10-year risk <10%; thus, 10-year risk assessment in people with 0 to 1 risk factor is not necessary.

After the LDL-C goal has been achieved, if the TG is still ≥200 mg/dL, non-HDL-C (total-C minus HDL-C) becomes a secondary target of therapy. Non-HDL-C goals are set 30 mg/dL higher than LDL-C goals for each risk category.

At the time of hospitalization for an acute coronary event, consideration can be given to initiating drug therapy at discharge if the LDL-C is ≥130 mg/dL (see NCEP Guidelines above).

Since the goal of treatment is to lower LDL-C, the NCEP recommends that LDL-C levels be used to initiate and assess treatment response. Only if LDL-C levels are not available, should the total-C be used to monitor therapy.

Although lovastatin may be useful to reduce elevated LDL-C levels in patients with combined hypercholesterolemia and hypertriglyceridemia where hypercholesterolemia is the major abnormality (Type IIb hyperlipoproteinemia), it has not been studied in conditions where the major abnormality is elevation of chylomicrons, VLDL or IDL (i.e., hyperlipoproteinemia types I, III, IV, or V). ***

The NCEP classification of cholesterol levels in pediatric patients with a familial history of hypercholesterolemia or premature cardiovascular disease is summarized below:

Category | Total-C (mg/dL) | LDL-C (mg/dL)
Acceptable | <170 | <110
Borderline | 170 to 199 | 110 to 129
High | ≥200 | ≥130

Children treated with lovastatin in adolescence should be re-evaluated in adulthood and appropriate changes made to their cholesterol-lowering regimen to achieve adult goals for LDL-C.

CONTRAINDICATIONS

Hypersensitivity to any component of this medication.

Active liver disease or unexplained persistent elevations of serum transaminases (see WARNINGS).

Concomitant administration with strong CYP3A4 inhibitors (e.g., itraconazole, ketoconazole, posaconazole, voriconazole, HIV protease inhibitors, boceprevir, telaprevir, erythromycin, clarithromycin, telithromycin ,nefazodone, and cobicistat-containing products) (see WARNINGS, Myopathy/Rhabdomyolysis) .

Pregnancy and lactation. (see PRECAUTIONS, Pregnancyand Nursing Mothers). Atherosclerosis is a chronic process and the discontinuation of lipid-lowering drugs during pregnancy should have little impact on the outcome of long-term therapy of primary hypercholesterolemia. Moreover, cholesterol and other products of the cholesterol biosynthesis pathway are essential components for fetal development, including synthesis of steroids and cell membranes. Because of the ability of inhibitors of HMG-CoA reductase such as lovastatin to decrease the synthesis of cholesterol and possibly other products of the cholesterol biosynthesis pathway, lovastatin is contraindicated during pregnancy and in nursing mothers. Lovastatin should be administered to women of childbearing age only when such patients are highly unlikely to conceive.If the patient becomes pregnant while taking this drug, lovastatin should be discontinued immediately and the patient should be apprised of the potential hazard to the fetus (see PRECAUTIONS, Pregnancy).

WARNINGS

Myopathy/Rhabdomyolysis

Lovastatin, like other inhibitors of HMG-CoA reductase, occasionally causes myopathy manifested as muscle pain, tenderness or weakness with creatine kinase (CK) above 10 times the upper limit of normal (ULN). Myopathy sometimes takes the form of rhabdomyolysis with or without acute renal failure secondary to myoglobinuria, and rare fatalities have occurred. The risk of myopathy is increased by high levels of HMG-CoA reductase inhibitory activity in plasma.

The risk of myopathy/rhabdomyolysis is dose related.In a clinical study (EXCEL) in which patients were carefully monitored and some interacting drugs were excluded, there was one case of myopathy among 4933 patients randomized to lovastatin 20 to 40 mg daily for 48 weeks, and 4 among 1649 patients randomized to 80 mg daily.

All patients starting therapy with lovastatin, or whose dose of lovastatin is being increased, should be advised of the risk of myopathy and told to report promptly any unexplained muscle pain, tenderness or weakness particularly if accompanied by malaise or fever or if muscle signs and symptoms persist after discontinuing Lovastatin. Lovastatin therapy should be discontinued immediately if myopathy is diagnosed or suspected.In most cases, muscle symptoms and CK increases resolved when treatment was promptly discontinued. Periodic CK determinations may be considered in patients starting therapy with lovastatin or whose dose is being increased, but there is no assurance that such monitoring will prevent myopathy.

Many of the patients who have developed rhabdomyolysis on therapy with lovastatin have had complicated medical histories, including renal insufficiency usually as a consequence of long-standing diabetes mellitus. Such patients merit closer monitoring. Lovastatin therapy should be discontinued if markedly elevated CPK levels occur or myopathy is diagnosed or suspected. Lovatsatin therapy should also be temporarily withheld in any patient experiencing an acute or serious condition predisposing to the development of renal failure secondary to rhabdomyolysis, e.g., sepsis; hypotension; major surgery; trauma; severe metabolic, endocrine, or electrolyte disorders; or uncontrolled epilepsy.

The risk of myopathy/rhabdomyolysis is increased by concomitant use of lovastatin with the following:

Strong inhibitors of CYP3A4:Lovastatin, like several other inhibitors of HMG-CoA reductase, is a substrate of cytochrome P450 3A4 (CYP3A4). Certain drugs which inhibit this metabolic pathway can raise the plasma levels of lovastatin and may increase the risk of myopathy. These include itraconazole, ketoconazole, and posaconazole, voriconazole, the macrolide antibiotics erythromycin and clarithromycin, the ketolide antibiotic telithromycin, HIV protease inhibitors, boceprevir, telaprevir, the antidepressant nefazodone, or cobicistat-containing products. Combination of these drugs with lovastatin is contraindicated. If short-term treatment with strong CYP3A4 inhibitors is unavoidable, therapy with lovastatin should be suspended during the course of treatment (see CONTRAINDICATIONS; PRECAUTIONS, Drug Interactions).

Gemfibrozil: The combined use of lovastatin with gemfibrozil should be avoided.

Other lipid-lowering drugs (other fibrates or≥1 g/day of niacin):Caution should be used when prescribing other fibrates or lipid-lowering doses (≥1 g/day) of niacin with lovastatin, as these agents can cause myopathy when given alone. The benefit of further alterations in lipid levels by the combined use of lovastatin with other fibrates or niacin should be carefully weighed against the potential risks of these combinations.

Cyclosporine: The use of lovastatin with cyclosporine should be avoided.

Danazol, diltiazem, dronedarone or verapamil with higher doses of lovastatin: The dose of lovastatin should not exceed 20 mg daily in patients receiving concomitant medication with danazol, diltiazem, dronedarone, or verapamil.The benefits of the use of lovastatin in patients receiving danazol, diltiazem, dronedarone, or verapamil should be carefully weighed against the risks of these combinations.

Amiodarone: The dose of lovastatin should not exceed 40 mg daily in patients receiving concomitant medication with amiodarone.The combined use of lovastatin at doses higher than 40 mg daily with amiodarone should be avoided unless the clinical benefit is likely to outweigh the increased risk of myopathy. The risk of myopathy/rhabdomyolysis is increased when amiodarone is used concomitantly with higher doses of a closely related member of the HMG-CoA reductase inhibitor class.

Colchicine:Cases of myopathy, including rhabdomyolysis, have been reported with lovastatin coadministered with colchicine, and caution should be exercised when prescribing lovastatin with colchicine (see PRECAUTIONS, Drug Interactions).

Ranolazine:The risk of myopathy, including rhabdomyolysis, may be increased by concomitant administration of ranolazine. Dose adjustment of lovastatin may be considered during coadministration with ranolazine.

Prescribing recommendations for interacting agents are summarized in Table VII(see also CLINICAL PHARMACOLOGY, Pharmacokinetics; PRECAUTIONS, Drug Interactions; DOSAGE AND ADMINISTRATION).

Immune-Mediated Necrotizing Myopathy

There have been rare reports of immune-mediated necrotizing myopathy (IMNM), an autoimmune myopathy, associated with statin use. IMNM is characterized by: proximal muscle weakness and elevated serum creatine kinase, which persist despite discontinuation of statin treatment; positive anti-HMG CoA reductase antibody; muscle biopsy showing necrotizing myopathy; and improvement with immunosuppressive agents. Additional neuomuscular and serologic testing may be necessary. Treatment with immunosuppressive agents may be required. Consider risk of IMNM carefully prior to initiation of a different statin. If therapy is initiated with a different statin, monitor for signs and symptoms of IMNM.

Liver Dysfunction

Persistent increases (to more than 3 times the upper limit of normal) in serum transaminases occurred in 1.9% of adult patients who received lovastatin for at least one year in early clinical trials (see ADVERSE REACTIONS).When the drug was interrupted or discontinued in these patients, the transaminase levels usually fell slowly to pretreatment levels. The increases usually appeared 3 to 12 months after the start of therapy with lovastatin, and were not associated with jaundice or other clinical signs or symptoms. There was no evidence of hypersensitivity. In the EXCEL study (see CLINICAL PHARMACOLOGY, Clinical Studies), the incidence of persistent increases in serum transaminases over 48 weeks was 0.1% for placebo, 0.1% at 20 mg/day, 0.9% at 40 mg/day, and 1.5% at 80 mg/day in patients on lovastatin. However, in post-marketing experience with lovastatin, symptomatic liver disease has been reported rarely at all dosages (see ADVERSE REACTIONS).

In AFCAPS/TexCAPS, the number of participants with consecutive elevations of either alanine aminotransferase (ALT) or aspartate aminotransferase (AST) (> 3 times the upper limit of normal), over a median of 5.1 years of follow-up, was not significantly different between the lovastatin and placebo groups (18 [0.6%] vs. 11 [0.3%]). The starting dose of lovastatin was 20 mg/day; 50% of the lovastatin treated participants were titrated to 40 mg/day at Week 18. Of the 18 participants on lovastatin with consecutive elevations of either ALT or AST, 11 (0.7%) elevations occurred in participants taking 20 mg/day, while 7 (0.4%) elevations occurred in participants titrated to 40 mg/day. Elevated transaminases resulted in discontinuation of 6 (0.2%) participants from therapy in the lovastatin group (n=3,304) and 4 (0.1%) in the placebo group (n=3,301).

It is recommended that liver enzyme tests be obtained prior to initiating therapy with Lovastatin and repeated as clinically indicated.

There have been rare postmarketing reports of fatal and non-fatal hepatic failure in patients taking statins, including lovastatin. If serious liver injury with clinical symptoms and/or hyperbilirubinemia or jaundice occurs during treatment with Lovastatin, promptly interrupt therapy. If an alternate etiology is not found do not restart Lovastatin.

The drug should be used with caution in patients who consume substantial quantities of alcohol and/or have a past history of liver disease. Active liver disease or unexplained transaminase elevations are contraindications to the use of lovastatin.

Moderate (less than three times the upper limit of normal) elevations of serum transaminases have been reported following therapy with lovastatin (see ADVERSE REACTIONS). These changes appeared soon after initiation of therapy with lovastatin, were often transient, were not accompanied by any symptoms and interruption of treatment was not required.

Precautions

General

Lovastatin may elevate creatine phosphokinase and transaminase levels (see WARNINGSand ADVERSE REACTIONS). This should be considered in the differential diagnosis of chest pain in a patient on therapy with lovastatin.

Homozygous Familial Hypercholesterolemia

Lovastatin is less effective in patients with the rare homozygous familial hypercholesterolemia, possibly because these patients have no functional LDL receptors. Lovastatin appears to be more likely to raise serum transaminases (see ADVERSE REACTIONS) in these homozygous patients.

Information for Patients

Patients should be advised about substances they should not take concomitantly with lovastatin and be advised to report promptly unexplained muscle pain, tenderness, or weakness particularly if accompanied by malaise or fever or if muscle signs and symptoms persist after discountinuing Lovastatin (see list below and WARNINGS, Myopathy/Rhabdomyolysis). Patients should also be advised to inform other physicians prescribing a new medication that they are taking lovastatin.

It is recommended that liver enzymes be checked before starting therapy, and if signs or symptoms of liver injury occur. All patients treated with Lovastatin should be advised to report promptly any symptoms that may indicate liver injury, including fatigue, anorexia, right upper abdominal discomfort, dark urine or jaundice.

Repackaged By / Distributed By: RemedyRepack Inc.

625 Kolter Drive, Indiana, PA 15701

(724) 465-8762

Drug Interactions

CYP3A4 Interactions

Lovastatin is metabolized by CYP3A4 but has no CYP3A4 inhibitory activity; therefore it is not expected to affect the plasma concentrations of other drugs metabolized by CYP3A4. Strong inhibitors of CYP3A4 (e.g., itraconazole, ketoconazole, posaconazole, voriconazole, clarithromycin, telithromycin, HIV protease inhibitors, boceprevir, telaprevir, nefazodone, erythromycin, and cobicistat-containing products), and grapefruit juice increase the risk of myopathy by reducing the elimination of lovastatin. (See CONTRAINDICATIONS, WARNINGS, Myopathy/Rhabdomyolysis, and CLINICAL PHARMACOLOGY, Pharmacokinetics.)

Interactions With Lipid-Lowering Drugs That Can Cause Myopathy When Given Alone

The risk of myopathy is also increased by the following lipid-lowering drugs that are not strong CYP3A4 inhibitors, but which can cause myopathy when given alone.

- See WARNINGS, Myopathy/Rhabdomyolysis.
- Gemfibrozil
- Other fibrates
- Niacin (nicotinic acid) (≥1 g/day)

Other drug interactions

Cyclosporine:The risk of myopathy/rhabdomyolysis is increased by concomitant administration of cyclosporine (see WARNINGS, Myopathy/Rhabdomyolysis).

Danazol, Diltiazem, Dronedarone, or Verapamil:The risk of myopathy/rhabdomyolysis is increased by concomitant administration of danazol, diltiazem, dronedarone or verapamil particularly with higher doses of lovastatin (see WARNINGS, Myopathy/Rhabdomyolysis; CLINICAL PHARMACOLOGY, Pharmacokinetics).

Amiodarone:The risk of myopathy/rhabdomyolysis is increased when amiodarone is used concomitantly with a closely related member of the HMG-CoA reductase inhibitor class (see WARNINGS, Myopathy/Rhabdomyolysis).

Coumarin Anticoagulants: In a small clinical trial in which lovastatin was administered to warfarin treated patients; no effect on prothrombin time was detected. However, another HMG-CoA reductase inhibitor has been found to produce a less than two seconds increase in prothrombin time in healthy volunteers receiving low doses of warfarin. Also, bleeding and/or increased prothrombin time have been reported in a few patients taking coumarin anticoagulants concomitantly with lovastatin. It is recommended that in patients taking anticoagulants, prothrombin time be determined before starting lovastatin and frequently enough during early therapy to insure that no significant alteration of prothrombin time occurs. Once a stable prothrombin time has been documented, prothrombin times can be monitored at the intervals usually recommended for patients on coumarin anticoagulants. If the dose of lovastatin is changed, the same procedure should be repeated. Lovastatin therapy has not been associated with bleeding or with changes in prothrombin time in patients not taking anticoagulants.

Colchicine:Cases of myopathy, including rhabdomyolysis, have been reported with lovastatin coadministered with colchicine. See WARNINGS, Myopathy/Rhabdomyolysis.

Ranolazine:The risk of myopathy, including rhabdomyolysis, may be increased by concomitant administration of ranolazine. See WARNINGS, Myopathy/Rhabdomyolysis.

Propranolol: In normal volunteers, there was no clinically significant pharmacokinetic or pharmacodynamic interaction with concomitant administration of single doses of lovastatin and propranolol.

Digoxin: In patients with hypercholesterolemia, concomitant administration of lovastatin and digoxin resulted in no effect on digoxin plasma concentrations.

Oral Hypoglycemic Agents: In pharmacokinetic studies of lovastatin in hypercholesterolemic non-insulin dependent diabetic patients, there was no drug interaction with glipizide or with chlorpropamide (see CLINICAL PHARMACOLOGY, Clinical Studies).

Endocrine Function

Increases in HbA1c and fasting serum glucose levels have been reported with HMG-CoA reductase inhibitors, including Lovastatin.

HMG-CoA reductase inhibitors interfere with cholesterol synthesis and as such might theoretically blunt adrenal and/or gonadal steroid production. Results of clinical trials with drugs in this class have been inconsistent with regard to drug effects on basal and reserve steroid levels. However, clinical studies have shown that lovastatin does not reduce basal plasma cortisol concentration or impair adrenal reserve, and does not reduce basal plasma testosterone concentration. Another HMG-CoA reductase inhibitor has been shown to reduce the plasma testosterone response to HCG. In the same study, the mean testosterone response to HCG was slightly but not significantly reduced after treatment with lovastatin 40 mg daily for 16 weeks in 21 men. The effects of HMG-CoA reductase inhibitors on male fertility have not been studied in adequate numbers of male patients. The effects, if any, on the pituitary-gonadal axis in premenopausal women are unknown. Patients treated with lovastatin who develop clinical evidence of endocrine dysfunction should be evaluated appropriately. Caution should also be exercised if an HMG-CoA reductase inhibitor or other agent used to lower cholesterol levels is administered to patients also receiving other drugs (e.g., spironolactone, cimetidine) that may decrease the levels or activity of endogenous steroid hormones.

CNS Toxicity

Lovastatin produced optic nerve degeneration (Wallerian degeneration of retinogeniculate fibers) in clinically normal dogs in a dose-dependent fashion starting at 60 mg/kg/day, a dose that produced mean plasma drug levels about 30 times higher than the mean drug level in humans taking the highest recommended dose (as measured by total enzyme inhibitory activity). Vestibulocochlear Wallerian-like degeneration and retinal ganglion cell chromatolysis were also seen in dogs treated for 14 weeks at 180 mg/kg/day, a dose which resulted in a mean plasma drug level (Cmax) similar to that seen with the 60 mg/kg/day dose.

CNS vascular lesions, characterized by perivascular hemorrhage and edema, mononuclear cell infiltration of perivascular spaces, perivascular fibrin deposits and necrosis of small vessels, were seen in dogs treated with lovastatin at a dose of 180 mg/kg/day, a dose which produced plasma drug levels (Cmax) which were about 30 times higher than the mean values in humans taking 80 mg/day.

Similar optic nerve and CNS vascular lesions have been observed with other drugs of this class.

Cataracts were seen in dogs treated for 11 and 28 weeks at 180 mg/kg/day and 1 year at 60 mg/kg/day.

Carcinogenesis, Mutagenesis, Impairment of Fertility

In a 21-month carcinogenic study in mice, there was a statistically significant increase in the incidence of hepatocellular carcinomas and adenomas in both males and females at 500 mg/kg/day. This dose produced a total plasma drug exposure 3 to 4 times that of humans given the highest recommended dose of lovastatin (drug exposure was measured as total HMG-CoA reductase inhibitory activity in extracted plasma). Tumor increases were not seen at 20 and 100 mg/kg/day, doses that produced drug exposures of 0.3 to 2 times that of humans at the 80 mg/day dose. A statistically significant increase in pulmonary adenomas was seen in female mice at approximately 4 times the human drug exposure. (Although mice were given 300 times the human dose [HD] on a mg/kg body weight basis, plasma levels of total inhibitory activity were only 4 times higher in mice than in humans given 80 mg of lovastatin.)

There was an increase in incidence of papilloma in the non-glandular mucosa of the stomach of mice beginning at exposures of 1 to 2 times that of humans. The glandular mucosa was not affected. The human stomach contains only glandular mucosa.

In a 24-month carcinogenicity study in rats, there was a positive dose response relationship for hepatocellular carcinogenicity in males at drug exposures between 2 to 7 times that of human exposure at 80 mg/day (doses in rats were 5, 30 and 180 mg/kg/day).

An increased incidence of thyroid neoplasms in rats appears to be a response that has been seen with other HMG-CoA reductase inhibitors.

A chemically similar drug in this class was administered to mice for 72 weeks at 25, 100, and 400 mg/kg body weight, which resulted in mean serum drug levels approximately 3, 15, and 33 times higher than the mean human serum drug concentration (as total inhibitory activity) after a 40 mg oral dose. Liver carcinomas were significantly increased in high dose females and mid- and high dose males, with a maximum incidence of 90 percent in males. The incidence of adenomas of the liver was significantly increased in mid- and high dose females. Drug treatment also significantly increased the incidence of lung adenomas in mid- and high dose males and females. Adenomas of the Harderian gland (a gland of the eye of rodents) were significantly higher in high dose mice than in controls.

No evidence of mutagenicity was observed in a microbial mutagen test using mutant strains of Salmonella typhimuriumwith or without rat or mouse liver metabolic activation. In addition, no evidence of damage to genetic material was noted in an in vitroalkaline elution assay using rat or mouse hepatocytes, a V-79 mammalian cell forward mutation study, an in vitrochromosome aberration study in CHO cells, or an in vivochromosomal aberration assay in mouse bone marrow.

Drug-related testicular atrophy, decreased spermatogenesis, spermatocytic degeneration and giant cell formation were seen in dogs starting at 20 mg/kg/day. Similar findings were seen with another drug in this class. No drug-related effects on fertility were found in studies with lovastatin in rats. However, in studies with a similar drug in this class, there was decreased fertility in male rats treated for 34 weeks at 25 mg/kg body weight, although this effect was not observed in a subsequent fertility study when this same dose was administered for 11 weeks (the entire cycle of spermatogenesis, including epididymal maturation). In rats treated with this same reductase inhibitor at 180 mg/kg/day, seminiferous tubule degeneration (necrosis and loss of spermatogenic epithelium) was observed. No microscopic changes were observed in the testes from rats of either study. The clinical significance of these findings is unclear.

Pregnancy

Pregnancy Category X

See CONTRAINDICATIONS.

Safety in pregnant women has not been established.

Lovastatin has been shown to produce skeletal malformations in offspring of pregnant mice and rats dosed during gestation at 80 mg/kg/day (affected mouse fetuses/total: 8/307 compared to 4/289 in the control group; affected rat fetuses/total: 6/324 compared to 2/308 in the control group). Female rats dosed before mating through gestation at 80 mg/kg/day also had fetuses with skeletal malformations (affected fetuses/total: 1/152 compared to 0/171 in the control group). The 80 mg/kg/day dose in mice is 7 times the human dose based on body surface area and in rats results in 5 times the human exposure based on AUC. In pregnant rats given doses of 2, 20, or 200 mg/kg/day and treated through lactation, the following effects were observed: neonatal mortality (4.1%, 3.5%, and 46%, respectively, compared to 0.6% in the control group), decreased pup body weights throughout lactation (up to 5%, 8%, and 38%, respectively, below control), supernumerary ribs in dead pups (affected fetuses/total: 0/7, 1/17, and11/79, respectively, compared to 0/5 in the control group), delays in ossification in dead pups (affected fetuses/total: 0/7, 0/17, and 1/79, respectively, compared to 0/5 in the control group) and delays in pup development (delays in the appearance of an auditory startle response at 200 mg/kg/day and free-fall righting reflexes at 20 and 200 mg/kg/day).

Direct dosing of neonatal rats by subcutaneous injection with 10 mg/kg/day of the open hydroxyacid form of lovastatin resulted in delayed passive avoidance learning in female rats (mean of 8.3 trials to criterion, compared to 7.3 and 6.4 in untreated and vehicle-treated controls; no effects on retention 1 week later) at exposures 4 times the human systemic exposure at 80 mg/day based on AUC. No effect was seen in male rats. No evidence of malformations was observed when pregnant rabbits were given 5 mg/kg/day (doses equivalent to a human dose of 80 mg/day based on body surface area) or a maternally toxic dose of 15 mg/kg/day (3 times the human dose of 80 mg/day based on body surface area).

Rare clinical reports of congenital anomalies following intrauterine exposure to HMG-CoA reductase inhibitors have been received. However, in an analysis† of greater than 200 prospectively followed pregnancies exposed during the first trimester to lovastatin or another closely related HMG-CoA reductase inhibitor, the incidence of congenital anomalies was comparable to that seen in the general population. This number of pregnancies was sufficient to exclude a 3-fold or greater increase in congenital anomalies over the background incidence.

____________________________________

3 Manson, J.M., Freyssinges, C., Ducrocq, M.B., Stephenson, W.P., Postmarketing Surveillance of Lovastatin and Simvastatin Exposure During Pregnancy. Reproductive Toxicology. 10(6):439-446. 1996.

Maternal treatment with lovastatin may reduce the fetal levels of mevalonate, which is a precursor of cholesterol biosynthesis. Atherosclerosis is a chronic process, and ordinarily discontinuation of lipid-lowering drugs during pregnancy should have little impact on the long-term risk associated with primary hypercholesterolemia. For these reasons, lovastatin should not be used in women who are pregnant, or can become pregnant (see CONTRAINDICATIONS). Lovastatin should be administered to women of childbearing potential only when such patients are highly unlikely to conceive and have been informed of the potential hazards. Treatment should be immediately discontinued as soon as pregnancy is recognized.

Nursing Mothers

It is not known whether lovastatin is excreted in human milk. Because a small amount of another drug in this class is excreted in human breast milk and because of the potential for serious adverse reactions in nursing infants, women taking lovastatin should not nurse their infants (see CONTRAINDICATIONS).

Pediatric Use

Safety and effectiveness in patients 10 to 17 years of age with heFH have been evaluated in controlled clinical trials of 48 weeks duration in adolescent boys and controlled clinical trials of 24 weeks duration in girls who were at least 1 year post-menarche. Patients treated with lovastatin had an adverse experience profile generally similar to that of patients treated with placebo. Doses greater than 40 mg have not been studied in this population.In these limited controlled studies, there was no detectable effect on growth or sexual maturation in the adolescent boys or on menstrual cycle length in girls. See CLINICAL PHARMACOLOGY, Clinical Studies in Adolescent Patients; ADVERSE REACTIONS, Adolescent Patients; and DOSAGE AND ADMINISTRATION, Adolescent Patients (10 to 17 years of age) with Heterozygous Familial Hypercholesterolemia. Adolescent females should be counseled on appropriate contraceptive methods while on lovastatin therapy (see CONTRAINDICATIONSand PRECAUTIONS, Pregnancy). Lovastatin has not been studied in pre-pubertal patients or patients younger than 10 years of age.

Geriatric Use

A pharmacokinetic study with lovastatin showed the mean plasma level of HMG-CoA reductase inhibitory activity to be approximately 45% higher in elderly patients between 70 to 78 years of age compared with patients between 18 to 30 years of age; however, clinical study experience in the elderly indicates that dosage adjustment based on this age-related pharmacokinetic difference is not needed. In the two large clinical studies conducted with lovastatin (EXCEL and AFCAPS/TexCAPS), 21% (3094/14850) of patients were ≥65 years of age. Lipid-lowering efficacy with lovastatin was at least as great in elderly patients compared with younger patients, and there were no overall differences in safety over the 20 to 80 mg/day dosage range (see CLINICAL PHARMACOLOGY). Lovastatin should be prescribed with caution in the elderly.

ADVERSE REACTIONS

Phase III Clinical Studies

In Phase III controlled clinical studies involving 613 patients treated with lovastatin, the adverse experience profile was similar to that shown below for the 8,245-patient EXCEL study (see Expanded Clinical Evaluation of Lovastatin [EXCEL] Study).

Persistent increases of serum transaminases have been noted (see WARNINGS, Liver Dysfunction). About 11% of patients had elevations of CK levels of at least twice the normal value on one or more occasions. The corresponding values for the control agent cholestyramine was 9 percent. This was attributable to the noncardiac fraction of CK. Large increases in CK have sometimes been reported (see WARNINGS, Myopathy/Rhabdomyolysis).

Expanded Clinical Evaluation of Lovastatin (EXCEL) Study

Lovastatin was compared to placebo in 8,245 patients with hypercholesterolemia (total-C 240-300 mg/dL [6.2-7.8 mmol/L]) in the randomized, double-blind, parallel, 48-week EXCEL study. Clinical adverse experiences reported as possibly, probably or definitely drug-related in ≥1% in any treatment group are shown in the table below. For no event was the incidence on drug and placebo statistically different.

 | Placebo (N=1663) % | Lovastatin 20 mg q.p.m. (N=1642) % | Lovastatin 40 mg q.p.m. (N=1645) % | Lovastatin 20 mg b.i.d. (N=1646) % | Lovastatin 40 mg b.i.d. (N=1649) %
Body As a Whole
Asthenia | 1.4 | 1.7 | 1.4 | 1.5 | 1.2
Gastrointestinal
Abdominal pain | 1.6 | 2.0 | 2.0 | 2.2 | 2.5
Constipation | 1.9 | 2.0 | 3.2 | 3.2 | 3.5
Diarrhea | 2.3 | 2.6 | 2.4 | 2.2 | 2.6
Dyspepsia | 1.9 | 1.3 | 1.3 | 1.0 | 1.6
Flatulence | 4.2 | 3.7 | 4.3 | 3.9 | 4.5
Nausea | 2.5 | 1.9 | 2.5 | 2.2 | 2.2
Musculoskeletal
Muscle cramps | 0.5 | 0.6 | 0.8 | 1.1 | 1.0
Myalgia | 1.7 | 2.6 | 1.8 | 2.2 | 3.0
Nervous System/Psychiatric
Dizziness | 0.7 | 0.7 | 1.2 | 0.5 | 0.5
Headache | 2.7 | 2.6 | 2.8 | 2.1 | 3.2
Skin
Rash | 0.7 | 0.8 | 1.0 | 1.2 | 1.3
Special Senses
Blurred vision | 0.8 | 1.1 | 0.9 | 0.9 | 1.2

Other clinical adverse experiences reported as possibly, probably or definitely drug-related in 0.5 to 1.0 percent of patients in any drug-treated group are listed below. In all these cases the incidence on drug and placebo was not statistically different. Body as a Whole:chest pain; Gastrointestinal:acid regurgitation, dry mouth, vomiting; Musculoskeletal:leg pain, shoulder pain, arthralgia; Nervous System/Psychiatric:insomnia, paresthesia; Skin:alopecia, pruritus; Special Senses:eye irritation.

In the EXCEL study (see CLINICAL PHARMACOLOGY, Clinical Studies), 4.6% of the patients treated up to 48 weeks were discontinued due to clinical or laboratory adverse experiences which were rated by the investigator as possibly, probably or definitely related to therapy with lovastatin. The value for the placebo group was 2.5%.

Air Force/Texas Coronary Atherosclerosis Prevention Study (AFCAPS/TexCAPS)

In AFCAPS/TexCAPS (see CLINICAL PHARMACOLOGY, Clinical Studies) involving 6,605 participants treated with 20 to 40 mg/day of lovastatin (n=3,304) or placebo (n=3,301), the safety and tolerability profile of the group treated with lovastatin was comparable to that of the group treated with placebo during a median of 5.1 years of follow-up. The adverse experiences reported in AFCAPS/TexCAPS were similar to those reported in EXCEL (see ADVERSE REACTIONS, Expanded Clinical Evaluation of Lovastatin (EXCEL) Study).

Concomitant Therapy

In controlled clinical studies in which lovastatin was administered concomitantly with cholestyramine, no adverse reactions peculiar to this concomitant treatment were observed. The adverse reactions that occurred were limited to those reported previously with lovastatin or cholestyramine. Other lipid-lowering agents were not administered concomitantly with lovastatin during controlled clinical studies. Preliminary data suggests that the addition of gemfibrozil to therapy with lovastatin is not associated with greater reduction in LDL-C than that achieved with lovastatin alone. In uncontrolled clinical studies, most of the patients who have developed myopathy were receiving concomitant therapy with cyclosporine, gemfibrozil or niacin (nicotinic acid). The combined use of lovastatin with cyclosporine or gemfibrozil should be avoided. Caution should be used when prescribing other fibrates or lipid-lowering doses (≥1 g/day) of niacin with lovastatin (see WARNINGS, Myopathy/Rhabdomyolysis).

The following effects have been reported with drugs in this class. Not all the effects listed below have necessarily been associated with lovastatin therapy.

Skeletal: muscle cramps, myalgia, myopathy, rhabdomyolysis, arthralgias.

There have been rare reports of immune-mediated necrotizing myopathy associated with statin use [see WARNINGS, Myopathy/Rhabdomyolysis].

Neurological: dysfunction of certain cranial nerves (including alteration of taste, impairment of extra-ocular movement, facial paresis), tremor, dizziness, vertigo, paresthesia, peripheral neuropathy, peripheral nerve palsy, psychic disturbances, anxiety, insomnia, depression.

There have been rare postmarketing reports of cognitive impairment (e.g., memory loss, forgetfulness, amnesia, memory impairment, confusion) associated with statin use. These cognitive issues have been reported for all statins. The reports are generally nonserious, and reversible upon statin discontinuation, with variable times to symptom onset (1 day to years) and symptom resolution (median of 3 weeks).

Hypersensitivity Reactions: An apparent hypersensitivity syndrome has been reported rarely which has included one or more of the following features: anaphylaxis, angioedema, lupus erythematous-like syndrome, polymyalgia rheumatica, dermatomyositis, vasculitis, purpura, thrombocytopenia, leukopenia, hemolytic anemia, positive ANA, ESR increase, eosinophilia, arthritis, arthralgia, urticaria, asthenia, photosensitivity, fever, chills, flushing, malaise, dyspnea, toxic epidermal necrolysis, erythema multiforme, including Stevens-Johnson syndrome.

Gastrointestinal: pancreatitis, hepatitis, including chronic active hepatitis, cholestatic jaundice, fatty change in liver; and rarely, cirrhosis, fulminant hepatic necrosis, and hepatoma; anorexia, vomiting, fatal and non-fatal hepatic failure.

Skin: alopecia, pruritus. A variety of skin changes (e.g., nodules, discoloration, dryness of skin/mucous membranes, changes to hair/nails) have been reported.

Reproductive: gynecomastia, loss of libido, erectile dysfunction.

Eye: progression of cataracts (lens opacities), ophthalmoplegia.

Laboratory Abnormalities: elevated transaminases, alkaline phosphatase, γ-glutamyl transpeptidase, and bilirubin; thyroid function abnormalities.

Respiratory: interstitial lung disease

Adolescent Patients (ages 10 to 17 years)

In a 48-week controlled study in adolescent boys with heFH (n=132) and a 24-week controlled study in girls who were at least 1 year post-menarche with heFH (n=54), the safety and tolerability profile of the groups treated with lovastatin (10 to 40 mg daily) was generally similar to that of the groups treated with placebo (see CLINICAL PHARMACOLOGY, Clinical Studies in Adolescent Patientsand PRECAUTIONS, Pediatric Use).

OVERDOSAGE

After oral administration of lovastatin to mice, the median lethal dose observed was >15 g/m^2.

Five healthy human volunteers have received up to 200 mg of lovastatin as a single dose without clinically significant adverse experiences. A few cases of accidental overdosage have been reported; no patients had any specific symptoms, and all patients recovered without sequelae. The maximum dose taken was 5 to 6 g.

Until further experience is obtained, no specific treatment of overdosage with lovastatin can be recommended.

The dialyzability of lovastatin and its metabolites in man is not known at present.

Dosage and Administration

The patient should be placed on a standard cholesterol-lowering diet before receiving lovastatin and should continue on this diet during treatment with lovastatin (see NCEP Treatment Guidelines for details on dietary therapy). Lovastatin should be given with meals.

Adult Patients

The usual recommended starting dose is 20 mg once a day given with the evening meal. The recommended dosing range is 10 to 80 mg/day in single or two divided doses; the maximum recommended dose is 80 mg/day. Doses should be individualized according to the recommended goal of therapy (see NCEP Guidelines and CLINICAL PHARMACOLOGY). Patients requiring reductions in LDL-C of 20% or more to achieve their goal (see INDICATIONS AND USAGE) should be started on 20 mg/day of lovastatin. A starting dose of 10 mg may be considered for patients requiring smaller reductions. Adjustments should be made at intervals of 4 weeks or more.

Cholesterol levels should be monitored periodically and consideration should be given to reducing the dosage of lovastatin if cholesterol levels fall significantly below the targeted range.

Dosage in Patients taking Danazol, Diltiazem, Dronedarone, or Verapamil

In patients taking danazol, diltiazem, dronedarone or verapamil concomitantly with lovastatin, therapy should begin with 10 mg of lovastatin and should not exceed 20 mg /day (see CLINICAL PHARMACOLOGY, Pharmacokinetics, WARNINGS, Myopathy/Rhabdomyolysis, PRECAUTIONS, Drug Interactions, Other Drug Interactions).

Dosage in Patients taking Amiodarone

In patients taking amiodarone concomitantly with lovastatin, the dose should not exceed 40 mg/day (see WARNINGS, Myopathy/Rhabdomyolysisand PRECAUTIONS, Drug Interactions, Other drug interactions).

Adolescent Patients (10 to 17 years of age) with Heterozygous Familial Hypercholesterolemia

The recommended dosing range is 10 to 40 mg/day; the maximum recommended dose is 40 mg/day. Doses should be individualized according to the recommended goal of therapy (see NCEP Pediatric Panel Guidelines ††, CLINICAL PHARMACOLOGY, and INDICATIONS AND USAGE). Patients requiring reductions in LDL-C of 20% or more to achieve their goal should be started on 20 mg/day of lovastatin. A starting dose of 10 mg may be considered for patients requiring smaller reductions. Adjustments should be made at intervals of 4 weeks or more.

Concomitant Lipid-Lowering Therapy

Lovastatin is effective alone or when used concomitantly with bile-acid sequestrants (see WARNINGS, Myopathy/Rhabdomyolysisand PRECAUTIONS, Drug Interactions).

Dosage in Patients with Renal Insufficiency

In patients with severe renal insufficiency (creatinine clearance <30 mL/min), dosage increases above 20 mg/day should be carefully considered and, if deemed necessary, implemented cautiously (see CLINICAL PHARMACOLOGYand WARNINGS, Myopathy/Rhabdomyolysis).

4 National Cholesterol Education Program (NCEP): Highlights of the Report of the Expert Panel on Blood Cholesterol Levels in Children and Adolescents. Pediatrics . 89(3): 495-501, 1992.

HOW SUPPLIED

Lovastatin Tablets USP (white to off white round, unscored tablets) containing 40mg of lovastatin and engraved with

“CTI 143"

NDC: 70518-2425-00

NDC: 70518-2425-01

PACKAGING: 30 in 1 BLISTER PACK

PACKAGING: 90 in 1 BOTTLE PLASTIC

Storage

Store at 20º to 25º C (68º to 77º F). [See USP Controlled Room Temperature.] Lovastatin Tablets must be protected from light and stored in a well-closed, light-resistant and child proof container.

Repackaged and Distributed By:

Remedy Repack, Inc.

625 Kolter Dr. Suite #4 Indiana, PA 1-724-465-8762

PRINCIPAL DISPLAY PANEL

DRUG: Lovastatin

GENERIC: Lovastatin

DOSAGE: TABLET

ADMINSTRATION: ORAL

NDC: 70518-2425-0

NDC: 70518-2425-1

COLOR: white

SHAPE: ROUND

SCORE: No score

SIZE: 10 mm

IMPRINT: CTI;143

PACKAGING: 30 in 1 BLISTER PACK

PACKAGING: 90 in 1 BOTTLE PLASTIC

ACTIVE INGREDIENT(S):

- LOVASTATIN 40mg in 1

INACTIVE INGREDIENT(S):

- LACTOSE MONOHYDRATE
- MAGNESIUM STEARATE
- CELLULOSE, MICROCRYSTALLINE
- POLOXAMER 188
- SODIUM STARCH GLYCOLATE TYPE A POTATO
- STARCH, CORN
- TALC
- BUTYLATED HYDROXYANISOLE